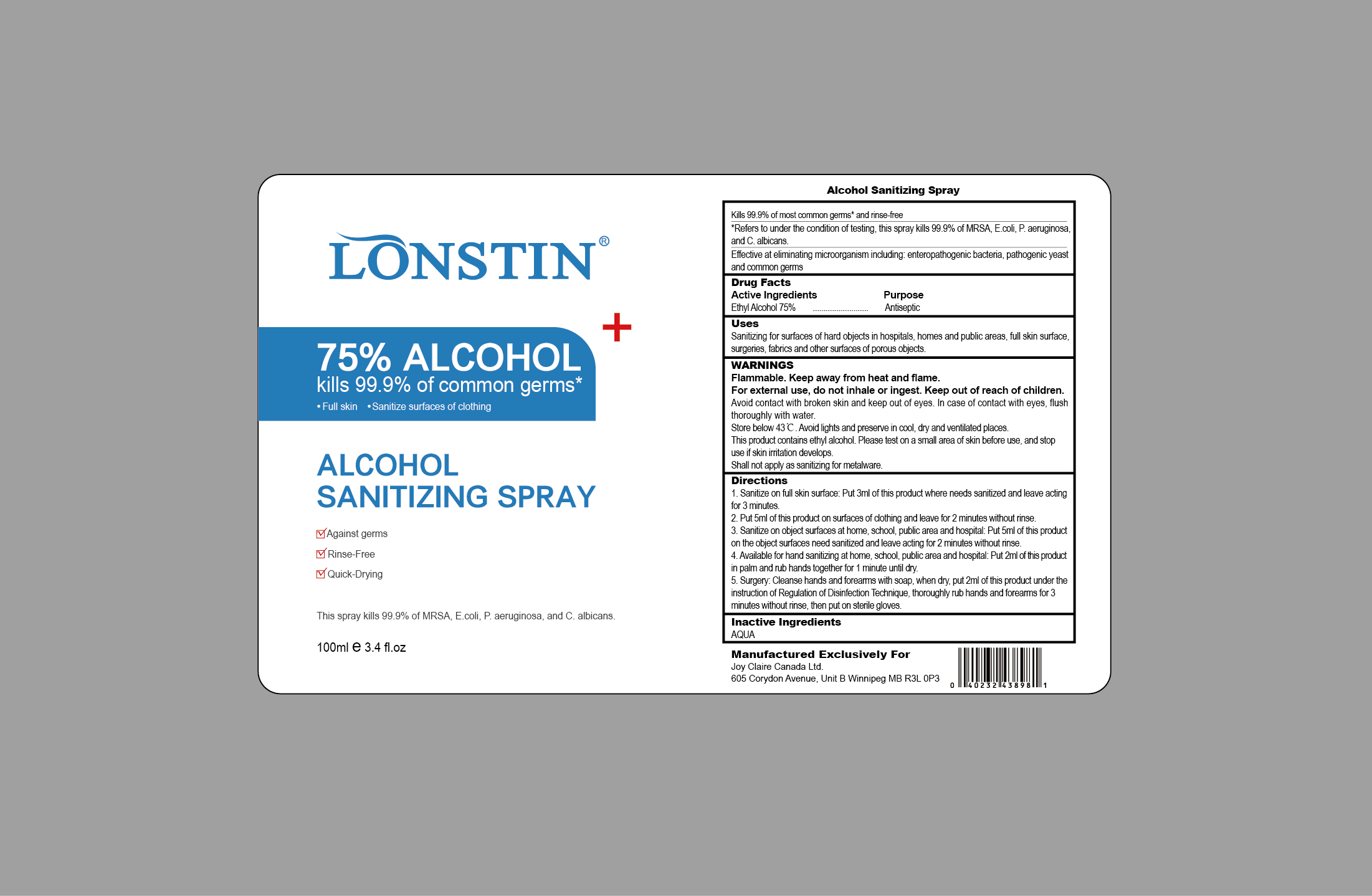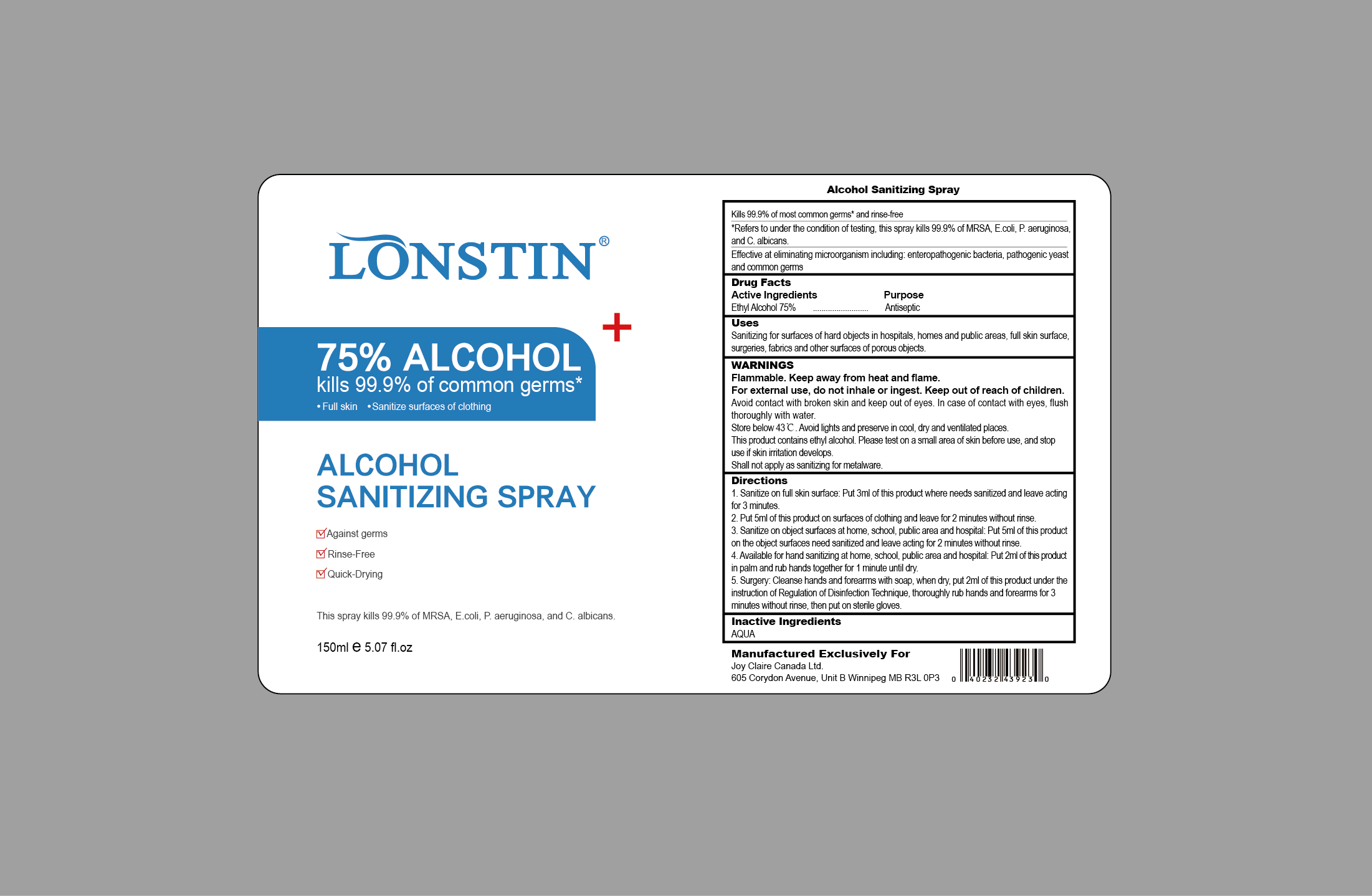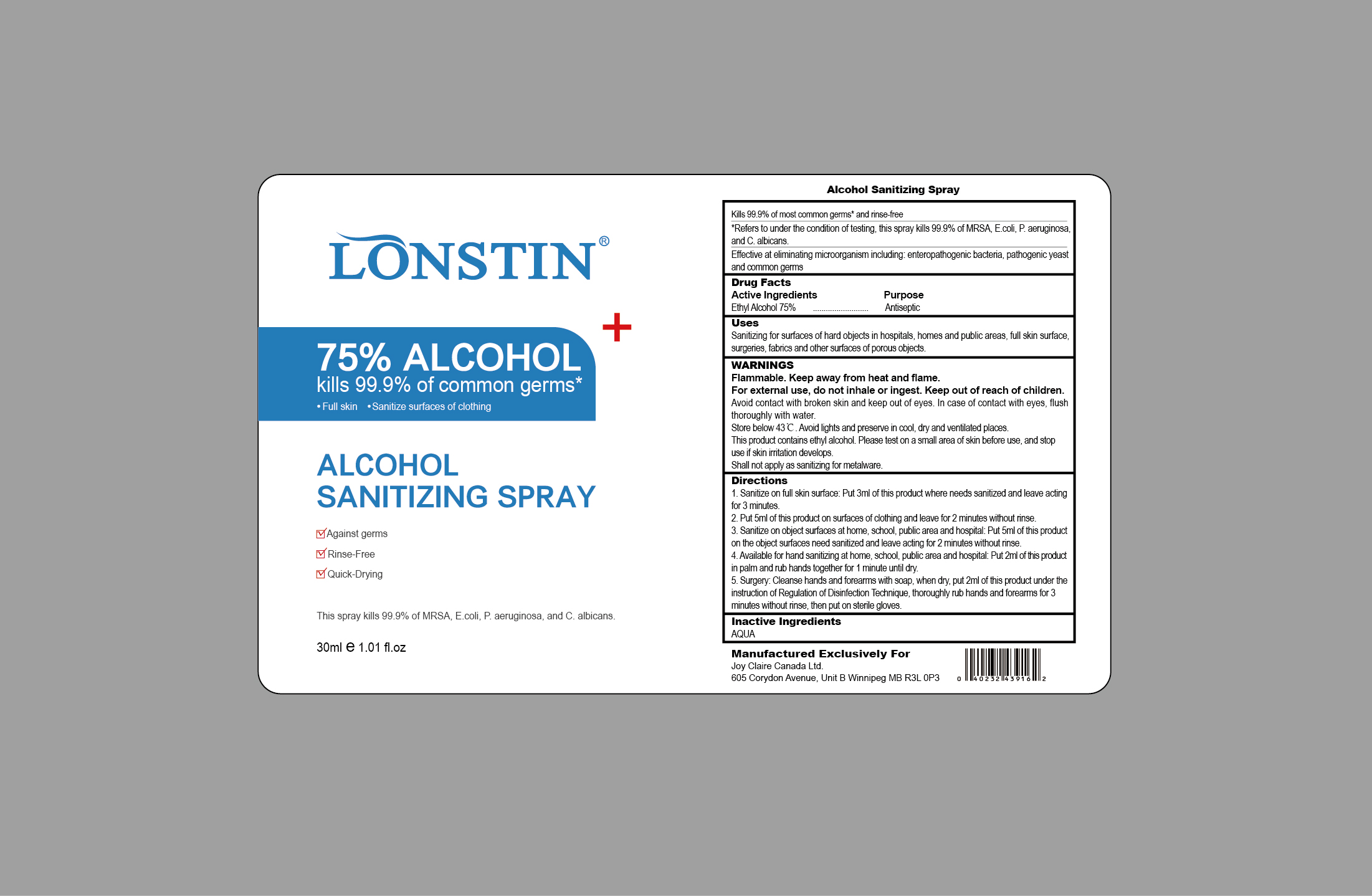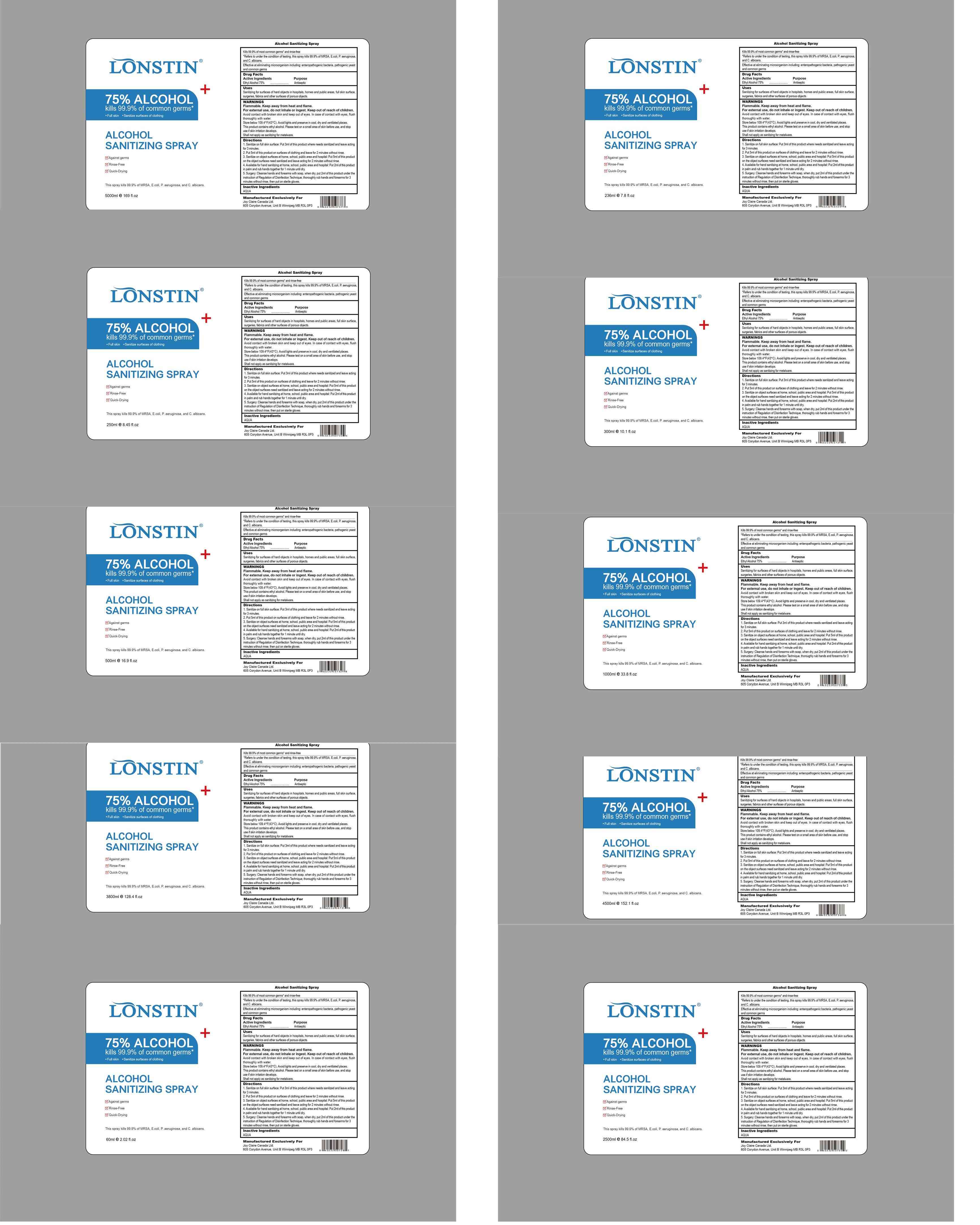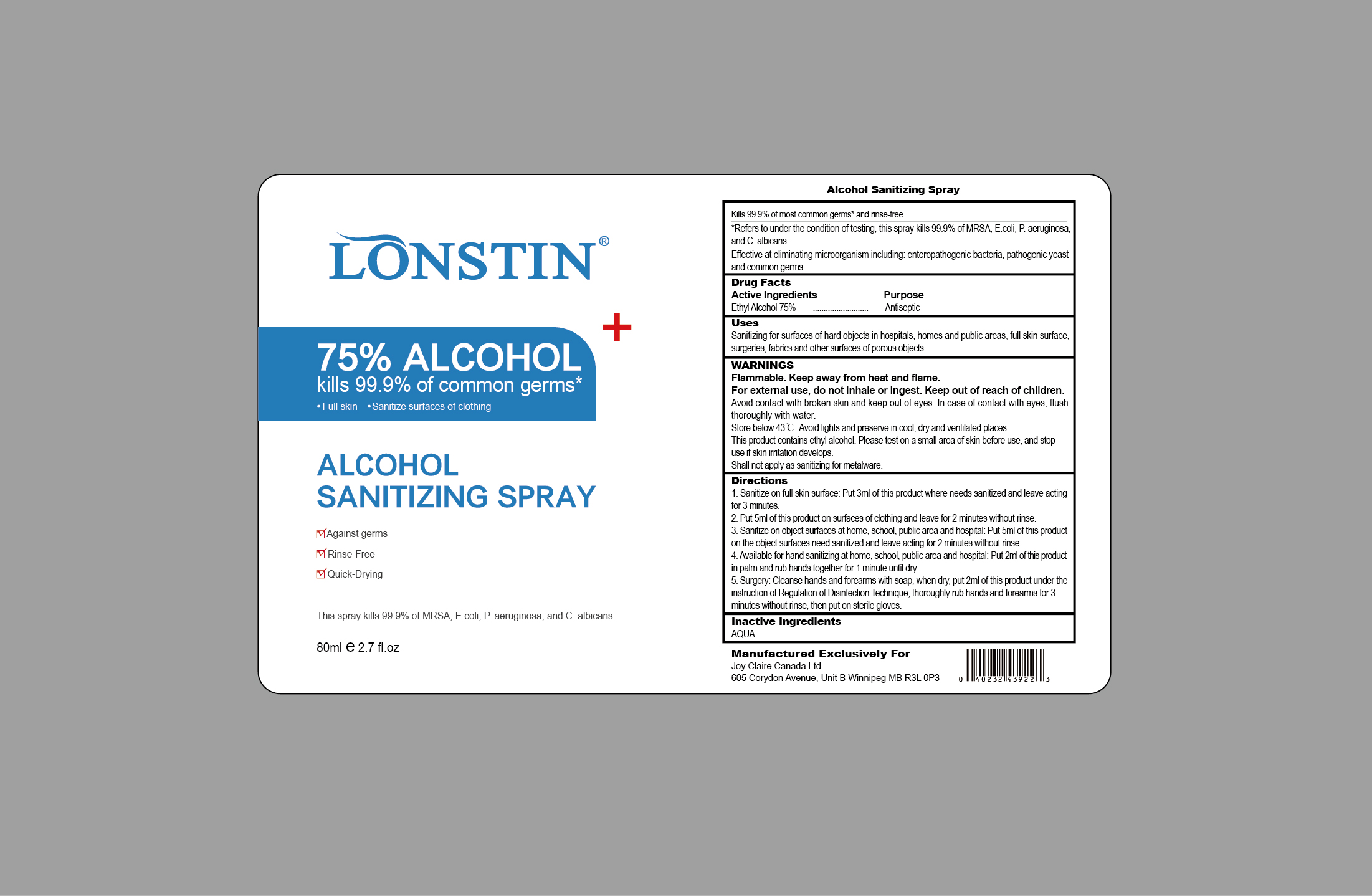 DRUG LABEL: Alcohol Sanitizing
NDC: 74743-011 | Form: SPRAY
Manufacturer: Guangzhou Joy Claire Biological Technology Co., Ltd
Category: otc | Type: HUMAN OTC DRUG LABEL
Date: 20200602

ACTIVE INGREDIENTS: ALCOHOL 75 mL/100 mL
INACTIVE INGREDIENTS: WATER

ALCOHOL SANITIZING SPRAY

Active Ingredients

Ethyl Alcohol 72.5%-77.5%(VM)

Purpose

Antiseptic

Uses

Sanitizing for surfaces of hard objects in hospitals,homes and public areas, full skin surface,

surgeries, fabrics and other surfaces of porous objects.

WARNINGS

Flammable.Keep away from heat and flame

For external use， do not inhale or ingest.Keep out of reach of children.

Avoid contact with broken skin and keep out of eyes.In case of contact with eyes， flush

thoroughly with water.

Store below 43℃.Avoid lights and preserve in cool， dry and ventilated places.

This product contains ethyl alcohol.Please test on a small area of skin before use， and stop

use if skin imtaion develops

Shall not apply as sanitizing for metalware.

Directions

1.Sanitize on full skin surface：Put 3ml of this product where needs sanitized and leave acting

for 3 minutes

2.Put 5ml of this product on surfaces of clothing and leave for 2 minutes without rinse

3.Sanitize on object surfaces at home， school， public area and hospital：Put 5ml of this product

on the object surfaces need sanitized and leave acting for 2 minutes without rinse

4.Available for hand sanitizing at home， school public area and hospital Put 2ml of this product

in palm and rub hands together for 1 minute until dry.

5.Surgery：Cleanse hands and forearms with soap， when dry， put 2ml of this product under the

instruction of Regulation of Disinfection Technique， thoroughly rub hands and forearms for 3

minutes without rinse， then put on sterile gloves.